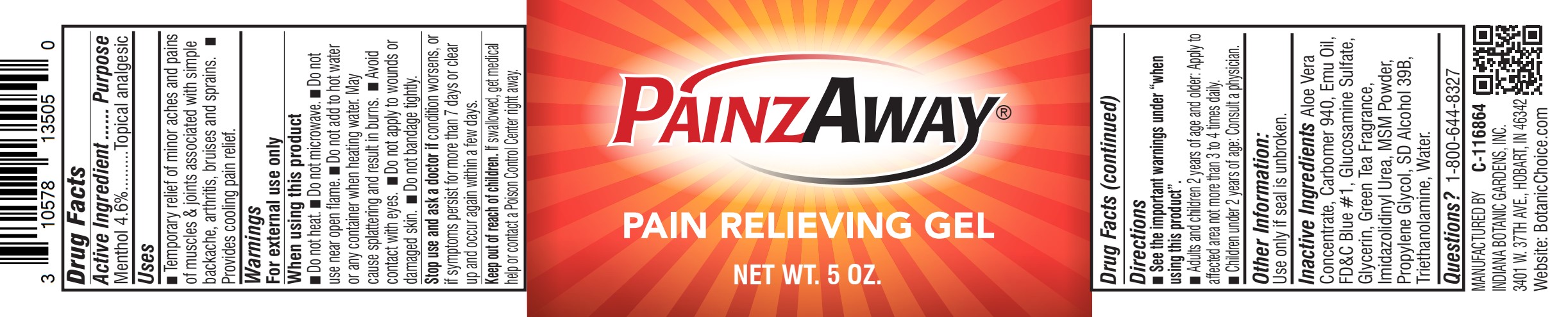 DRUG LABEL: Painzaway Pain Relieving Gel
NDC: 10578-135 | Form: GEL
Manufacturer: Indiana Botanic Gardens
Category: otc | Type: HUMAN OTC DRUG LABEL
Date: 20241213

ACTIVE INGREDIENTS: MENTHOL 4.6 g/100 g
INACTIVE INGREDIENTS: PROPYLENE GLYCOL; TROLAMINE; ALOE VERA LEAF; ALCOHOL; GLUCOSAMINE SULFATE; TEA LEAF OIL; IMIDUREA; WATER; CARBOMER 940; DIMETHYL SULFONE; FD&C BLUE NO. 1; EMU OIL; GLYCERIN

Painzaway Pain Relieving Gel

Active Ingredient

Menthol 4.6%

Purpose

topical analgesic

Uses

■ Temporary relief of minor aches and pains of muscles & joints associated with simple backache, arthritis, bruises and sprains. ■ Provides cooling pain relief.

Warnings

For external use only

When using this product

■ Do not heat ■ Do not microwave ■ Do not use near open flame ■ Do not add to hot water or any container when heating water. May cause splattering and result in burns. ■ Avoid contact with eyes ■ Do not apply to wounds or damaged skin ■ Do not bandage tightly

Stop use and ask a doctor if

condition worsens, or if symptoms persist for more than 7 days or clear up and occur again within a few days

Keep out of reach of children.

If swallowed, get medical help or contact a Poison Control Center right away.

Directions

■ See the important warnings under "when using this product"

■ Adults and children 2 years of age and older: apply to affected area not more than 3 to 4 times daily.

■ Children under 2 years of age: Consult a physician.

Other Information:

Use only if seal is unbroken.

Inactive Ingredients

Aloe Vera Concentrate, Carbomer 940, Emu Oil, FD&C Blue #1, Glucosamine Sulfate, Glycerin, Green Tea Fragrance, Imidazolidinyl Urea, MSM Powder, Propylene Glycol, SD Alcohol 39B, Triethanolamine, Water

Questions?

1-800-644-8327

MANUFACTURED BY
INDIANA BOTANIC GARDENS, INC.
3401 W. 37TH AVE., HOBART, IN 46342
Website: BotanicChoice.com

PACKAGE LABEL

PainzAway®

PAIN RELIEVING GEL

NET WT. 5 OZ.